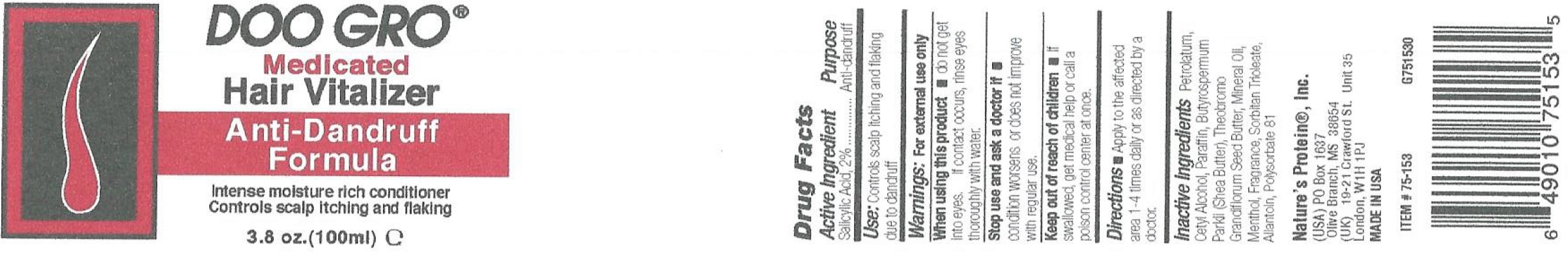 DRUG LABEL: Doo Gro Anti-Dandruff Vitalizer
NDC: 12022-006 | Form: OINTMENT
Manufacturer: J. Strickland & Co. DBA Nature's Protein, Inc.
Category: otc | Type: HUMAN OTC DRUG LABEL
Date: 20231031

ACTIVE INGREDIENTS: SALICYLIC ACID 20 mg/1 mL
INACTIVE INGREDIENTS: PETROLATUM; CETYL ALCOHOL; PARAFFIN; SHEA BUTTER; MINERAL OIL; MENTHOL; SORBITAN TRIOLEATE; ALLANTOIN; POLYSORBATE 81

Doo Gro Anti-Dandruff Ointment Vitalizer

Active Ingredient

salicylic Acid, 2%

Purpose

Anti-dandruff

Use:

Controls Scalp itching and flaking due to dandruff

Warnings:

For external use only

When using this product

- do not get into eyes. If contact occurs, rinse eyes thoroughly with water.

Stop use and ask a doctor if

- condition worsens or does not improve with regular use

Keep out of reach of children

- if swallowed, get medical help or call a poison control center at once.

Directions

- Apply to the affected area 1-4 times daily or as directed by a doctor.

Inactive Ingredients

Petrolatum, Cetyl Alcohol, Paraffin, Butyrospermum Parkii (Shea Butter), Theobromo Grandiflorum Seed Butter, Mineral Oil, Menthol, Fragrance, Sorbitan Trioleate, Allantoln, Polysorbate 81